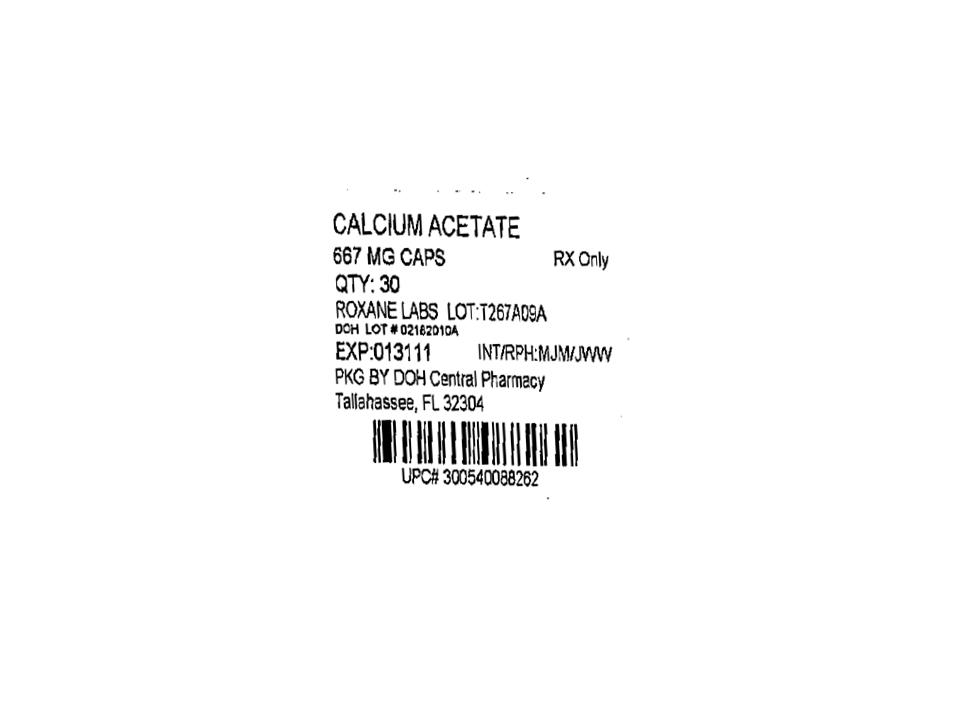 DRUG LABEL: Calcium Acetate
NDC: 53808-0216 | Form: CAPSULE
Manufacturer: State of Florida DOH Central Pharmacy
Category: prescription | Type: HUMAN PRESCRIPTION DRUG LABEL
Date: 20100312

ACTIVE INGREDIENTS: CALCIUM ACETATE 667 mg/1 1
INACTIVE INGREDIENTS: FD&C BLUE NO. 1; FD&C RED NO. 3; GELATIN; MAGNESIUM STEARATE; POLYETHYLENE GLYCOL 8000; TITANIUM DIOXIDE; ALCOHOL; FD&C BLUE NO. 2; FD&C RED NO. 40; FD&C YELLOW NO. 6; FERROSOFERRIC OXIDE; PROPYLENE GLYCOL; SHELLAC

Calcium Acetate Capsules

DESCRIPTION

Each white opaque/blue opaque gelcap contains 667 mg of calcium acetate, (anhydrous; Ca(CH3COO)2; MW=158.17 grams) equal to 169 mg (8.45 mEq) calcium. Each capsule also contains FD&C blue #1, FD&C red #3, gelatin, magnesium stearate, polyethylene glycol 8000, and titanium dioxide. In addition to the ingredients listed above, each capsule contains Opacode (Black) monogrammingink. Opacode (Black) contains ethanol, FD&C blue #2, FD&C red #40, FD&C yellow #6, iron oxide black, Nbutyl alcohol, propylene glycol, and shellac. Calcium Acetate Capsules are administered orally for the control of hyperphosphatemia in end stage renal failure.

CLINICAL PHARMACOLOGY

Patients with advanced renal insufficiency (creatinine clearance less than 30 mL/min) exhibit phosphate retention and some degree of hyperphosphatemia. The retention of phosphate plays a pivotal role in causing secondary hyperparathyroidism associated with osteodystrophy, and soft-tissue calcification. The mechanism by which phosphate retention leads to hyperparathyroidism is not clearly delineated. Therapeutic efforts directed toward the control of hyperphosphatemia include reduction in the dietary intake of phosphate, inhibition of absorption of phosphate in the intestine with phosphate binders, and removal of phosphate from the body by more efficient methods of dialysis. The rate of removal of phosphate by dietary manipulation or by dialysis is insufficient. Dialysis patients absorb 40% to 80% of dietary phosphorus. Therefore, the fraction of dietary phosphate absorbed from the diet needs to be reduced by using phosphate binders in most renal failure patients on maintenance dialysis. Calcium acetate when taken with meals, combines with dietary phosphate to form insoluble calcium phosphate which is excreted in the feces. Maintenance of serum phosphorus below 6.0 mg/dl is generally considered as a clinically acceptable outcome of treatment with phosphate binders. Calcium acetate is highly soluble at neutral pH, making the calcium readily available for binding to phosphate in the proximal small intestine. Orally administered calcium acetate from pharmaceutical dosage forms has been demonstrated to be systemically absorbed up to approximately 40% under fasting conditions and up to approximately 30% under nonfasting conditions. This range represents data from both healthy subjects and renal dialysis patients under various conditions.

INDICATIONS AND USAGE

Calcium Acetate Capsules are indicated for the control of hyperphosphatemia in end stage renal failure and do not promote aluminum absorption.

CONTRAINDICATIONS

Patients with hypercalcemia.

WARNINGS

Patients with end stage renal failure may develop hypercalcemia when given calcium with meals. No other calcium supplements should be given concurrently with calcium acetate capsules. Progressive hypercalcemia due to overdose of calcium acetate may be severe as to require emergency measures. Chronic hypercalcemia may lead to vascular calcification, and other soft-tissue calcification. The serum calcium level should be monitored twice weekly during the early dose adjustment period. Theserum calcium times phosphate (CaXP) product should not be allowedto exceed 66. Radiographic evaluation of suspect anatomical region may be helpful in early detection of soft-tissue calcification.

PRECAUTIONS

General

Excessive dosage of calcium acetate induces hypercalcemia; therefore, early in the treatment during dosage adjustment serum calcium should be determined twice weekly. Should hypercalcemia develop, the dosage should be reduced or the treatment discontinued immediately depending on the severity of hypercalcemia. Calcium acetate should not be given to patients on digitalis, because hypercalcemia may precipitate cardiac arrhythmias. Calcium acetate therapy should always be started at low dose and should not be increased without careful monitoring of serum calcium. An estimate of daily calcium intake should be made initially and the intake adjusted as needed. Serum phosphorus should also be determined periodically.

Information for patients

The patients should be informed about compliance with dosage instructions, adherence to instructions about diet and avoidance of the use of nonprescription antacids. Patients should be informed about the symptoms of hypercalcemia (see ADVERSE REACTIONS).

Drug interactions

Calcium acetate may decrease the bioavailability of tetracyclines.

Carcinogenesis, mutagenesis, impairment of fertility

Long-term animal studies have notbeen performed to evaluate the carcinogenic potential, mutagenicity, or effect on fertility of calcium acetate.

Teratogenic effects: Category C:

Animal reproduction studies have not been conducted with calcium acetate. It is not known whether calcium acetate can cause fetal harm when administered to a pregnant woman or can affect reproduction capacity. Calcium acetate should be given to a pregnant woman only if clearly needed.

Pediatric use

Safety and effectiveness in pediatric patients have not been established.

Geriatric use

Of the total number of subjects in clinical studies of calcium acetate (N=91), 25 percent were 65 and over, while 7 percent were 75 and over. No overall differences in safety or effectiveness were

observed between these subjects and younger subjects, and other reported clinical experience has not identified differences in responses between the elderly and younger patients, but greater sensitivity of some older individuals cannot be ruled out.

ADVERSE REACTIONS

In clinical studies, patients have occasionally experienced nausea during calcium acetate therapy. Hypercalcemia may occur during treatment with calcium acetate. Mild hypercalcemia (Ca>10.5 mg/dl) may be asymptomatic or manifest itself as constipation, anorexia, nausea and vomiting. More severe hypercalcemia (Ca>12 mg/dl) is associated with confusion, delirium, stupor and coma. Mild hypercalcemia is easily controlled by reducing the calcium acetate dose or temporarily discontinuing therapy. Severe hypercalcemia can be treated by acute hemodialysis and discontinuing calcium acetate therapy. Decreasing dialysate calcium concentration could reduce the incidence and severity of calcium acetate induced hypercalcemia. The long-term effect of calcium acetate on the progression of vascular or soft-tissue calcification has not been determined. Isolated cases of pruritus have been reported which may represent allergic reactions.

Overdosage

Administration of calcium acetate in excess of the appropriate daily dosage can cause severe hypercalcemia (see ADVERSE REACTIONS).

DOSAGE AND ADMINISTRATION

The recommended initial dose of calcium acetate capsules for the adult dialysis patient is 2 capsules with each meal. The dosage may be increased gradually to bring the serum phosphate value below 6 mg/dl, as long as hypercalcemia does not develop. Most patients require 3 to 4 capsules with each meal.

HOW SUPPLIED

Calcium Acetate Capsules are supplied as white opaque/blue opaque capsules imprinted with “54 215” on the cap and body.

They are supplied by State of Florida DOH Central Pharmacy as follows:

NDC | Strength | Quantity/Form | Color | Source NDC
53808-0216-1 | 667 mg | 30 Capsule | Blue Opaque | 0054-0088-26

STORAGE

Store at 20° to 25°C (68° to 77°F). [See USP Controlled Room Temperature.]

This product was Manufactured By:

Roxane Laboratories, Inc.

And Repackaged By:

State of Florida DOH Central Pharmacy
104-2 Hamilton Park Drive
Tallahassee, FL 32304
United States

Package Label - Calcium Acetate Capsules, 667 mg

53808-0216-1 - 30 Capsules

Rx Only

Roxane Laboratories, Inc.